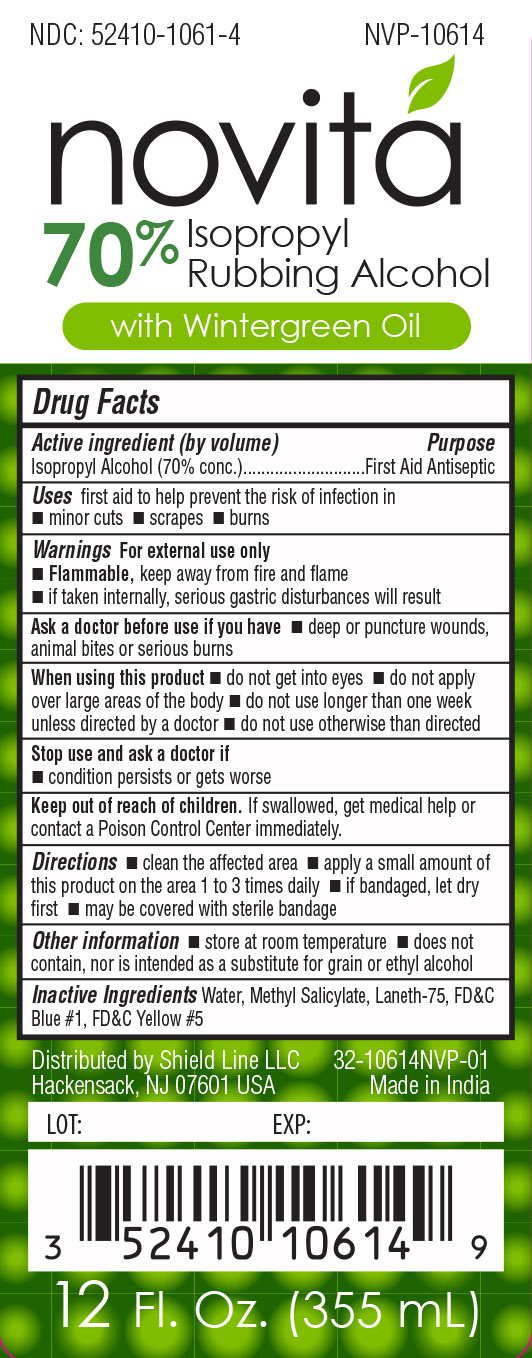 DRUG LABEL: NOVITA 70% ISOPROPYL RUBBING ALCOHOL WINTERGREEN
NDC: 52410-1061 | Form: LIQUID
Manufacturer: Shield Line LLC
Category: otc | Type: HUMAN OTC DRUG LABEL
Date: 20210224

ACTIVE INGREDIENTS: ISOPROPYL ALCOHOL 70 mL/100 mL
INACTIVE INGREDIENTS: WATER; PEG-75 LANOLIN; FD&C BLUE NO. 1; FD&C YELLOW NO. 5; METHYL SALICYLATE

Drug facts

Isopropyl Alcohol 70%(v/v)

PURPOSE

First Aid Antiseptic

Uses

first aid to help prevent the risk of infection in

- minor cuts
- scrapes
- burns

For external use only

- Flammable, keep away from fire and flame
- if taken internally, serious gastric disturbances will result

Ask a doctor before use if you have

- deep or puncture wounds, animal bites or serious burns

When using this product

- do not get into the eyes
- do not apply over large areas of the body
- do not use longer than a week unless directed by a doctor
- do not use otherwise than directed

Stop use and as a doctor if

- condition persists or gets worse

KEEP OUT OF REACH OF CHILDREN

If swallowed, get medical help or contact a Poison Control Center immediately

Directions

- clean the affected area
- apply a small amount of this product on the area 1 to 3 times daily
- if bandaged, lets dry first
- may be covered with a sterile bandage

Other information

- store at room temperature
- does not contain, nor is intended as a substitute for grain or ethyl alcohol

INACTIVE INGREDIENT

Water,Methyl Salicylate, Laneth-75, FD&C Blue#1, FD&C Yellow#5